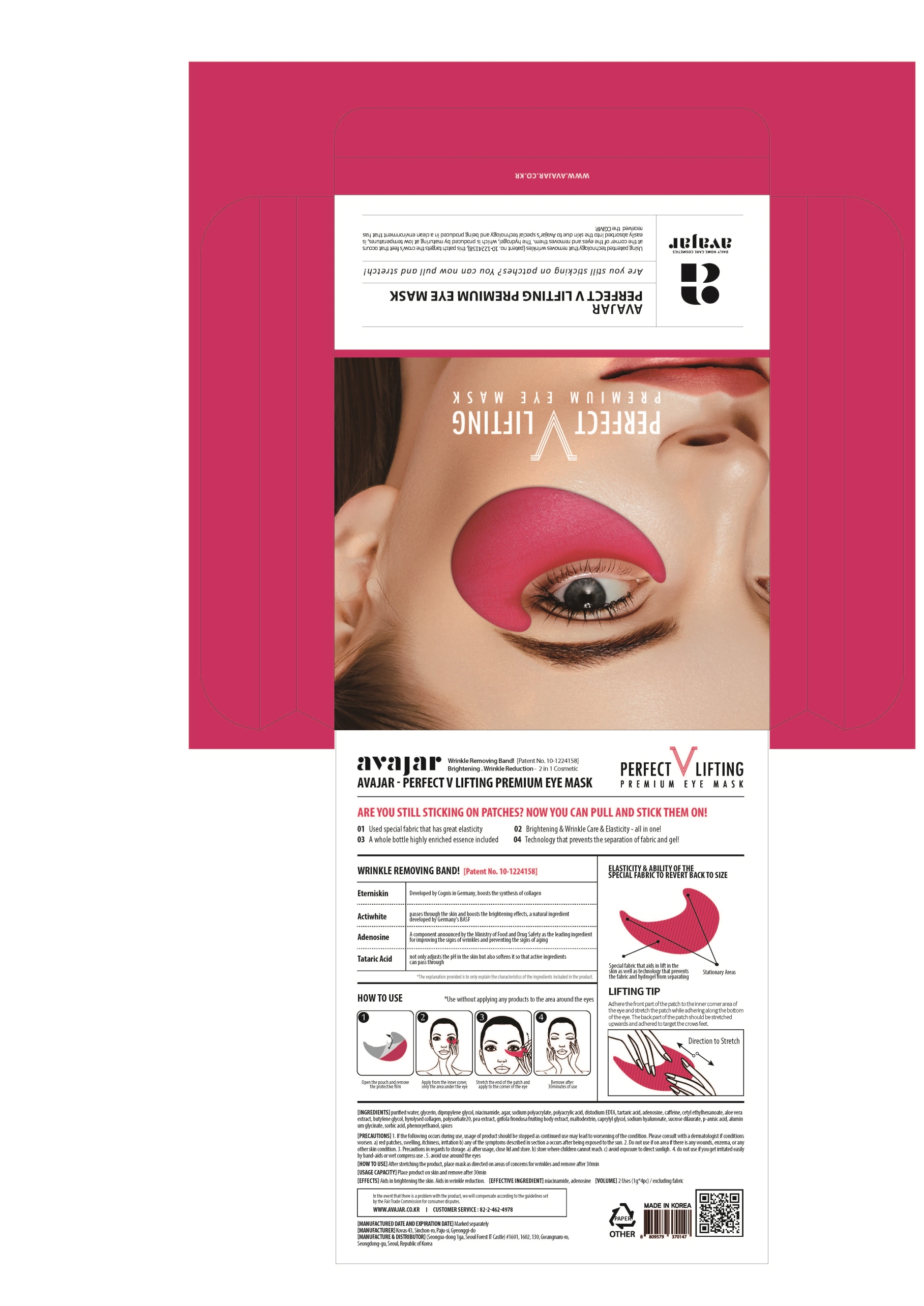 DRUG LABEL: Perfect V Lifting Premium Eye Mask
NDC: 71224-0005 | Form: LIQUID
Manufacturer: AVAJAR CO LTD
Category: otc | Type: HUMAN OTC DRUG LABEL
Date: 20180710

ACTIVE INGREDIENTS: GLYCERIN 30 g/100 g
INACTIVE INGREDIENTS: WATER; CAFFEINE; TARTARIC ACID; ADENOSINE

Drug Facts

ACTIVE INGREDIENT

Glycerin

INACTIVE INGREDIENT

Water, Tartaric Acid, Caffeine, Niacinamide, Adenosine, etc.

PURPOSE

Skin protectant: Anti-Wrinkle, Lifting

keep out of reach of the children

INDICATIONS AND USAGE

1. Open the pouch and remove the protective film.

2. Apply from the inner corner, only the area under the eye.

3. Stretch the end of the patch and apply to the corner of the eye.

4. Remove after 30 minutes of use.

DOSAGE AND ADMINISTRATION

for external use only

WARNINGS

1. If the following symptoms occur after product use, stop using the product immediately and consult a dermatologist (continuous use can exacerbate the symptoms).
1) Occurrence of red spots, swelling, itchiness, and other skin irritation
2) If the symptoms above occur after the application area is exposed to direct sunlight
2. Do not use on open wounds, eczema, and other skin irritations
3. Precaution for Storage and Handling
1) Close the lid after use
2) Keep out of reach of infants and children
3) Do not to store in a place with high/low temperature and exposed to direct sunlight